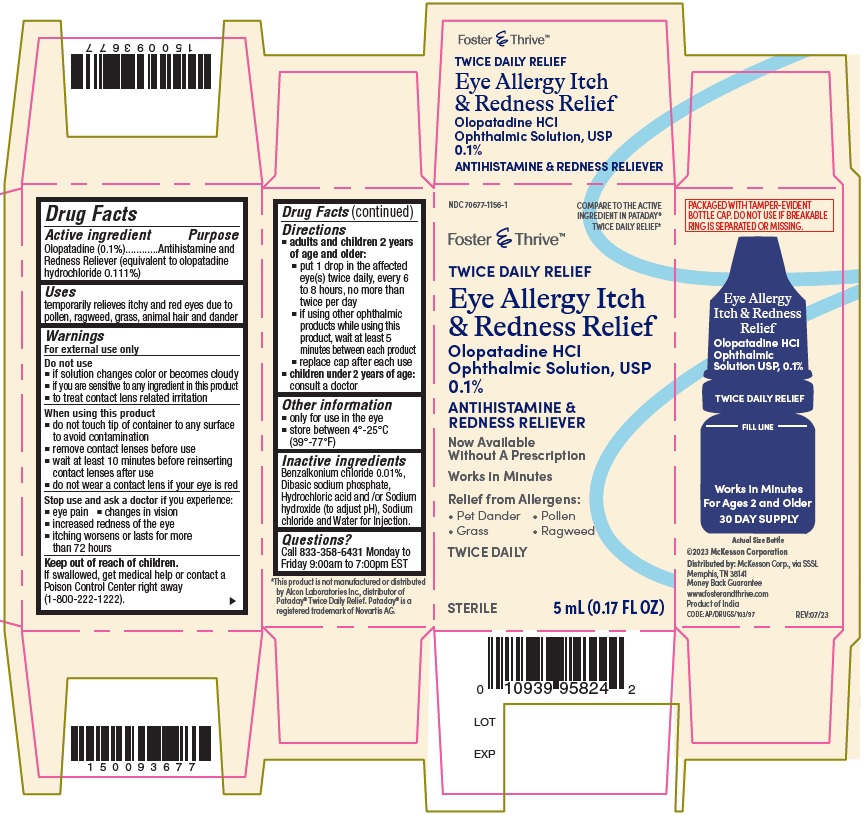 DRUG LABEL: Eye Allergy Itch and Redness Relief
NDC: 70677-1156 | Form: SOLUTION/ DROPS
Manufacturer: Strategic Sourcing Services LLC
Category: otc | Type: Human OTC Drug Label
Date: 20251210

ACTIVE INGREDIENTS: OLOPATADINE HYDROCHLORIDE 1 mg/1 mL
INACTIVE INGREDIENTS: BENZALKONIUM CHLORIDE; SODIUM PHOSPHATE, DIBASIC; HYDROCHLORIC ACID; SODIUM CHLORIDE; SODIUM HYDROXIDE; WATER

ACTIVE INGREDIENT

Olopatadine (0.1%) (equivalent to olopatadine hydrochloride 0.111%)

PURPOSE

Antihistamine and redness reliever

USES

temporarily relieves itchy and red eyes due to pollen, ragweed, grass, animal hair and dander

WARNINGS

For external use only

DO NOT USE

• if solution changes color or becomes cloudy
• if you are sensitive to any ingredient in this product
• to treat contact lens related irritation

WHEN USING THIS PRODUCT

- do not touch tip of container to any surface to avoid contamination
- remove contact lenses before use
- wait at least 10 minutes before reinserting contact lenses after use
- do not wear a contact lens if your eye is red

STOP USE AND ASK DOCTOR IF

you experience:

- eye pain
- changes in vision
- increased redness of the eye
- itching worsens or lasts for more than 72 hours

KEEP OUT OF REACH OF CHILDREN

If swallowed, get medical help or contact a Poison Control Center right away.

DIRECTIONS

• adults and children 2 years of age and older:
• put 1 drop in the affected eye(s) twice daily, every 6 to 8 hours, no more than twice per day
• if using other ophthalmic products while using this product, wait at least 5 minutes between each product
• replace cap after each use
• children under 2 years of age: consult a doctor

OTHER INFORMATION

• only for use in the eye
• store between 4° to 25°C (39° to 77°F)

INACTIVE INGREDIENTS

Benzalkonium chloride 0.01%, Dibasic sodium phosphate, Hydrochloric acid and /or Sodium hydroxide (to adjust pH), Sodium chloride and Water for Injection.

QUESTIONS?

Call 833-358-6431 Monday to Friday 9:00am to 7:00pm EST